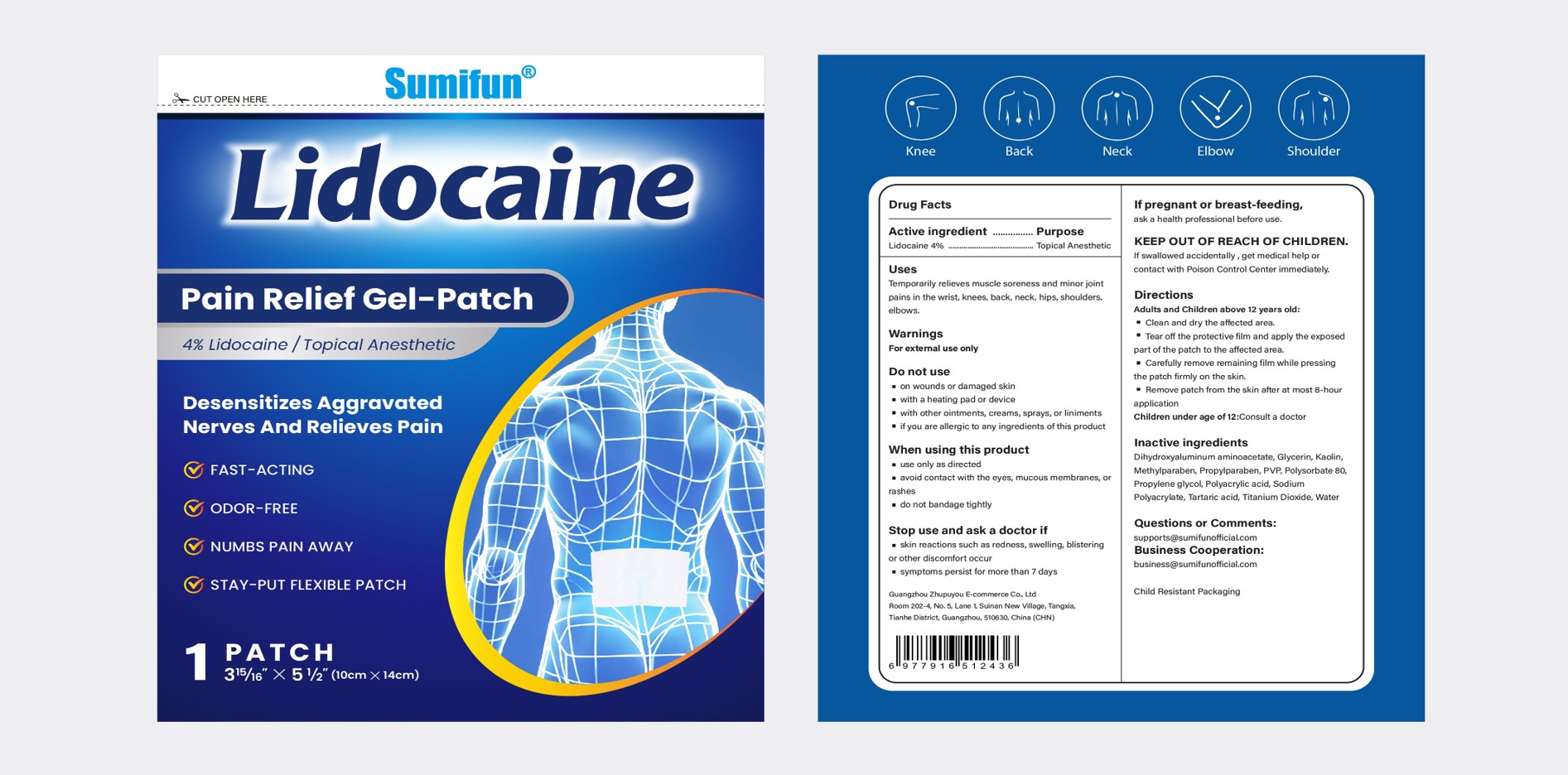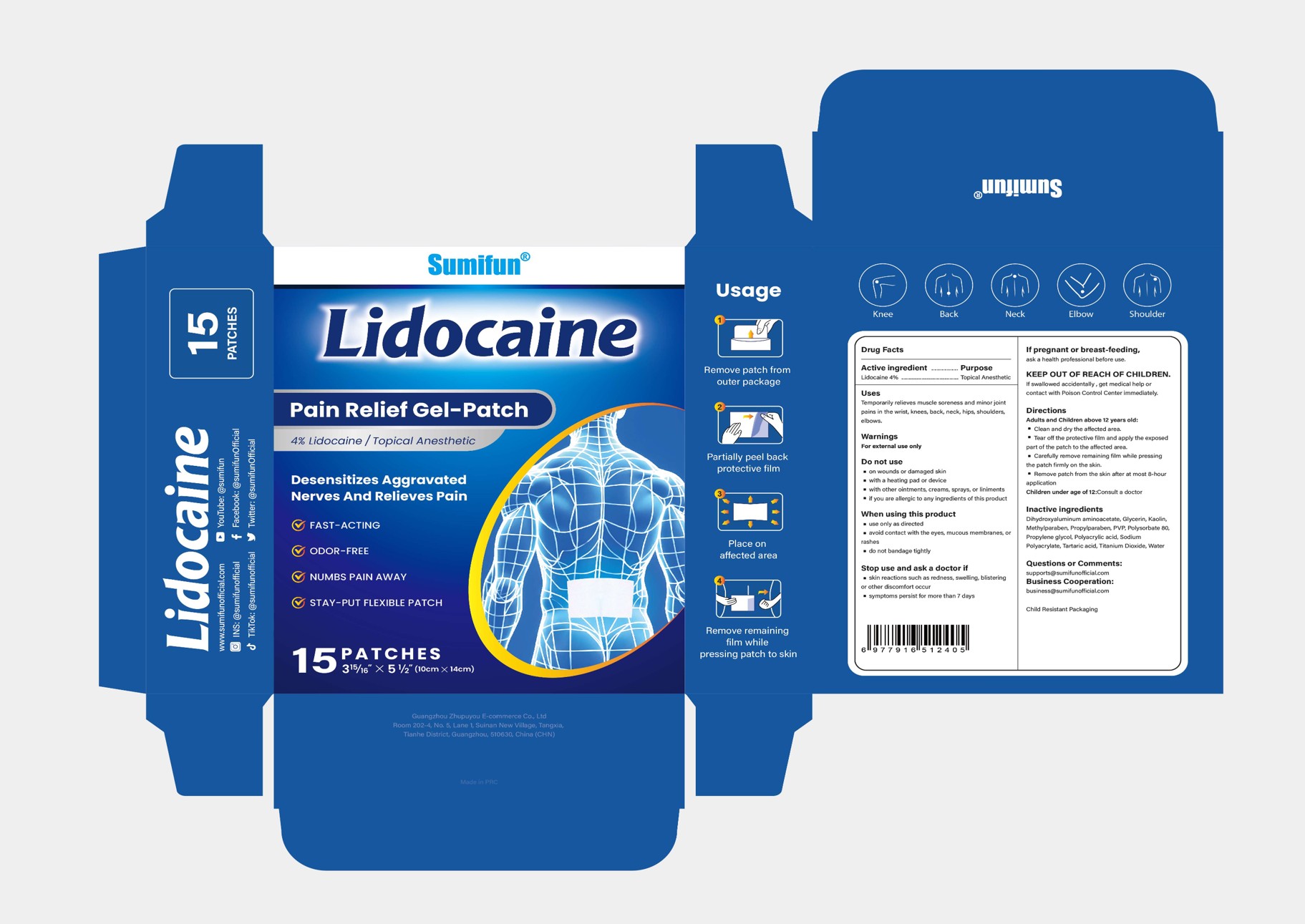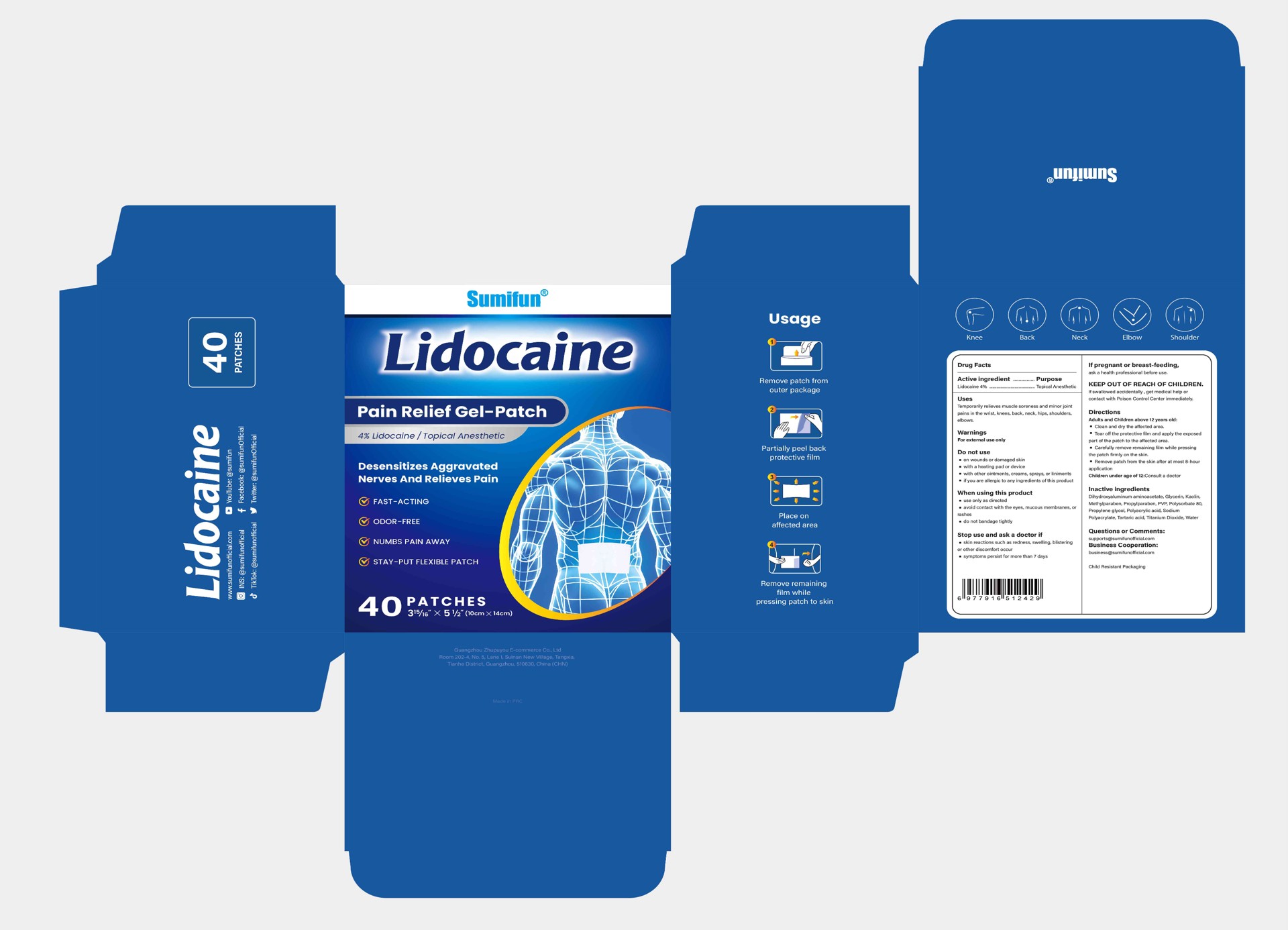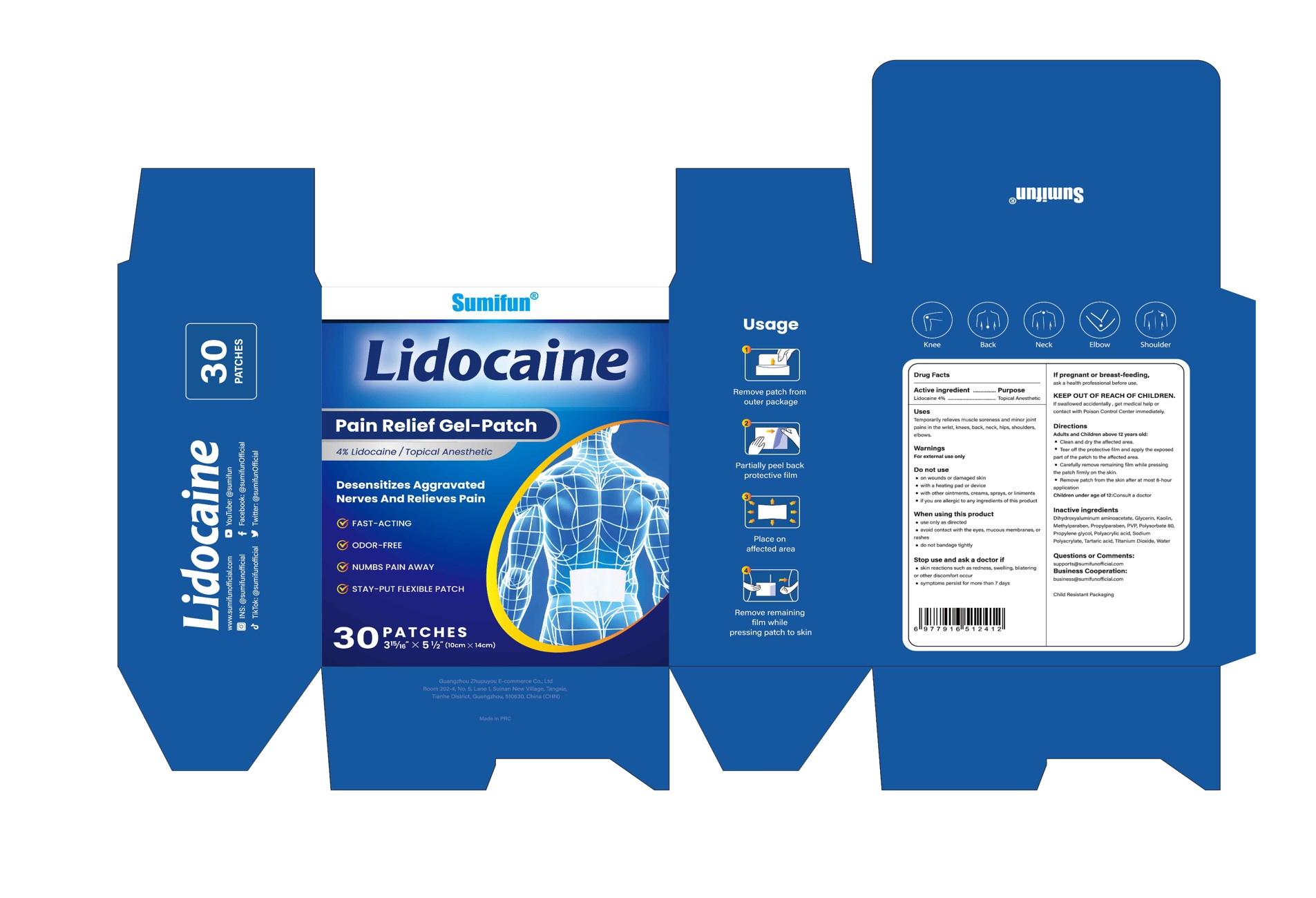 DRUG LABEL: Lidocaine Pain Relief Gel-Patch
NDC: 84165-106 | Form: PATCH
Manufacturer: Guangzhou Zhupuyou E-commerce Co., Ltd
Category: otc | Type: HUMAN OTC DRUG LABEL
Date: 20250115

ACTIVE INGREDIENTS: LIDOCAINE 0.04 g/1 g
INACTIVE INGREDIENTS: WATER; TITANIUM DIOXIDE; METHYLPARABEN; TARTARIC ACID; SODIUM POLYACRYLATE (2500000 MW); PROPYLPARABEN; POLYSORBATE 80; KAOLIN; GLYCERIN; DIHYDROXYALUMINUM AMINOACETATE; PVP; POLYACRYLIC ACID (250000 MW); PROPYLENE GLYCOL

Lidocaine Pain Relief Gel-Patch

Lidocaine Pain Relief Gel-Patch

ACTIVE INGREDIENT

Lidocaine 4%

PURPOSE

Topical Anesthetic

INDICATIONS AND USAGE

Temporarily relieves muscle soreness and minor jointpains in the wrist, knees, back, neck, hips, shoulders.elbows.

WARNINGS

For extemal use only

DO NOT USE

on wounds or damaged skin

with a heating pad or device

with other ointments, creams, sprays, or liniments

if you are allergic to any ingredients of this product

WHEN USING

use only as directed
avoid contact with the eyes, mucous membranes, or rashes
do not bandage tightly

STOP USE

skin reactions such as redness,swelling, blistering or other discomfort occur
symptoms persist for more than 7 days

KEEP OUT OF REACH OF CHILDREN

lf swallowed accidentally , get medical help orcontact with Poison Control Center immediately.

DOSAGE AND ADMINISTRATION

Adults and Children above 12 years old:
Clean and dry the affected area.
Tear off the protective film and apply the exposed part of the patch to the affected area.
Carefully remove remaining film while pressing the patch firmly on the skin
Remove patch from the skin after at most 8-hour application
Children under age of 12:Consult a doctor

INACTIVE INGREDIENT

Glycerin
Sodium Polyacrylate
Water
Methylparaben
Propylparaben
Dihydroxyaluminum aminoacetate
Tartaric acid
PVP
Polysorbate 80
Kaolin
Titanium Dioxide
Propylene glycol
Polyacrylic acid